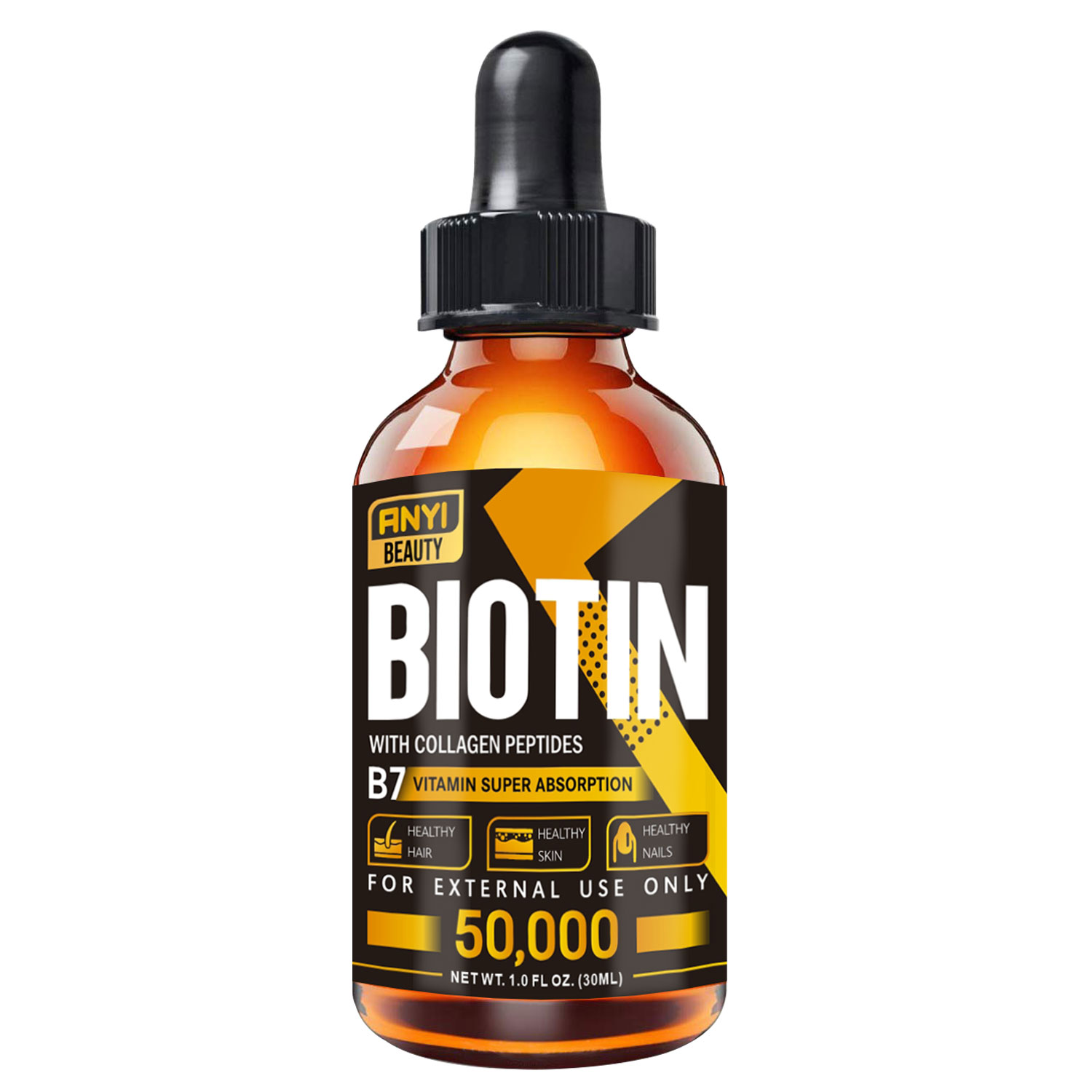 DRUG LABEL: Anyi Beauty Biotin With Collagen Peptides Oil
NDC: 84037-0110 | Form: OIL
Manufacturer: Guangzhou Zhicunxiu Cosmetics Co., Ltd
Category: otc | Type: HUMAN OTC DRUG LABEL
Date: 20240911

ACTIVE INGREDIENTS: CASTOR OIL 100 g/100 mL

Anyi Beauty Biotin With Collagen Peptides Oil

ACTIVE INGREDIENT

Castor Oil 100%

PURPOSE

Fade Scars & Stretch Marks
Thickens Eyelashes
Promotes Hair Growth
Use for Castor Oil Packs
Moisturizing Oil

INDICATIONS & USAGE

Fade Scars Stretch Marks
Thickens Eyelashes
Promotes Hair Growth
Use for Castor Oil Packs
Moisturizing Oil

WARNINGS

For external use only.keep away from flames and high heat. Keep out of reach of children. Discontinue useimmediately if redness oriratation occurs.

DOSAGE AND ADMINISTRATION

For external use only.keep away from flames and high heat. Keep out of reach of children. Discontinue useimmediately if redness oriratation occurs.

STORAGE AND HANDLING

Store at room temperature, away from light and in a cool place

STOP USE

Discontinue useimmediately if redness oriratation occurs.

INACTIVE INGREDIENT

none